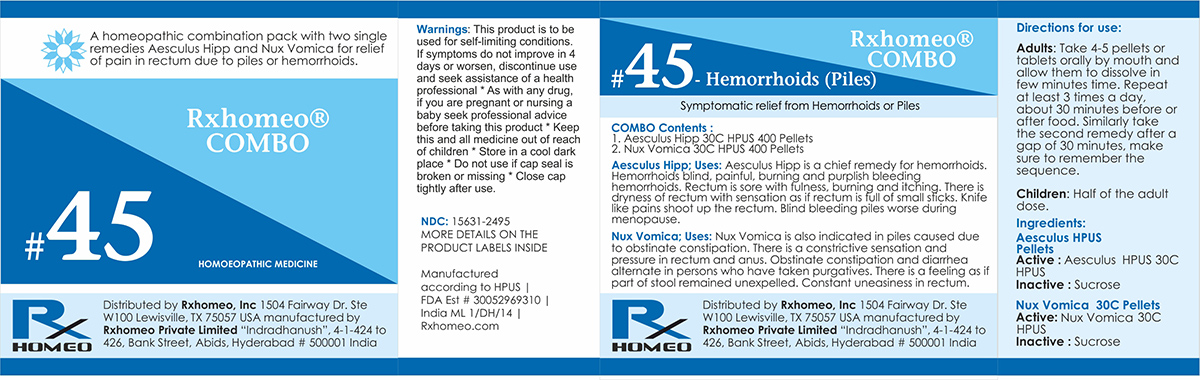 DRUG LABEL: Rxhomeo Homeopathic Combo-45
NDC: 15631-2495 | Form: KIT | Route: ORAL
Manufacturer: Rxhomeo Private Limited d.b.a.
Category: homeopathic | Type: HUMAN OTC DRUG LABEL
Date: 20161016

ACTIVE INGREDIENTS: HORSE CHESTNUT 2 [hp_X]/1 1; STRYCHNOS NUX-VOMICA SEED 3 [hp_X]/1 1
INACTIVE INGREDIENTS: SUCROSE; SUCROSE

ACTIVE INGREDIENT

AESCULUS HIPPOCASTANUM HPUS 2X and higher

NUX VOMICA HPUS 3X and higher

USES

A homeopathic combination pack with two single remedies Aesculus Hipp and Nux Vomica for relief of pain in rectum due to piles or hemorrhoids.

Aesculus Hipp;Uses: Aesculus Hipp is a chief remedy for hemorrhoids. Hemorrhoids blind, painful, burning and purplish bleeding hemorrhoids. Rectum is sore with fulness, burning and itching. There is dryness of rectum with sensation as if rectum is full of small sticks. Knife like pains shoot up the rectum. Blind bleeding piles worse during menopause.

Nux Vomica;Uses: Nux Vomica is also indicated in piles caused due to obstinate constipation. There is a constrictive sensation and pressure in rectum and anus. Obstinate constipation and diarrhea alternate in persons who have taken purgatives. There is a feeling as if part of stool remained unexpelled. Constant uneasiness in rectum.

INDICATIONS

Condition listed above or as directed by the physician

DOSAGE

PELLETS included in the Combo

Adults- Take 4 or 6 Pellets by mouth, three times daily or as suggested by physician. Children 2 years and older- take 1/2 the adult dose.

WARNINGS

This product is to be used for self-limiting conditions

STOP USE

If symptoms do not improve in 4 days, or worsen, discontinue use and seek assistance of health professional

KEEP OUT OF REACH OF CHILDREN

Keep this and all medication out of reach of children

Do not use if capseal is broken or missing.

Close the cap tightly after use.

INACTIVE INGREDIENTS

Sucrose for Pellets.

STORAGE

Store in a cool dark place

QUESTIONS OR COMMENTS

www.Rxhomeo.com | 1.888.2796642 | info@rxhomeo.com
Rxhomeo, Inc 1504 Fairway Dr. Ste W 100 Lewisville, TX 75057 USA